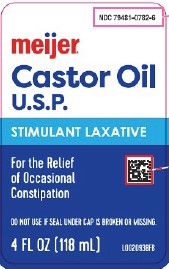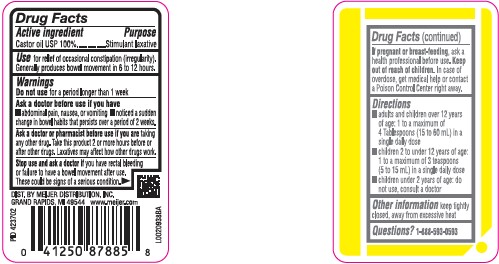 DRUG LABEL: Castor Oil
NDC: 79481-0782 | Form: LIQUID
Manufacturer: Meijer, Inc.
Category: otc | Type: HUMAN OTC DRUG LABEL
Date: 20260219

ACTIVE INGREDIENTS: CASTOR OIL 1000 mg/1 mL

Meijer 078.000/078AA
Castor Oil U.S.P.

Active ingredient

Castor oil USP 100%

Purpose

Stimulant laxative

Use

for relief of occasional constipation (irregularity). Generally produces bowel movement in 6 to 12 hours.

Warnings

for this product

Do not use

for a period longer than 1 week

Ask a doctor before use if you have

- abdominal pain, nausea, or vomiting
- noticed a sudden change in bowel habits that persists over a period of 2 weeks

Ask a doctor or pharmacist before use if you are

taking any other drug. Take this product 2 or more hours before or after other drugs. Laxatives may affect how other drugs work.

Stop use and ask a doctor

if you have rectal bleeding or failure to have a bowel movement after use. These could be signs of a serious condition.

If pregnant or breast-feeding,

ask a health professional before use.

Keep out of reach of children.

In case of overdose, get medical help or contact a Poison Control Center right away.

Directions

- adults and children over 12 years of age - 1 to a maximum of 4 Tablespoons (15 to 60 mL) in a single daily dose
- children 2 to under 12 years of age - 1 to a maximum of 3 teaspoons (5 to 15 mL) in a single daily dose
- children under 2 years of age - do not use, consult a doctor

Other Information

keep tightly closed, away from excessive heat

Questions?

1-888-593-0593

Invactive Ingredient

None

ADVERSE REACTION

DIST. BY MEIJER DISTRIBUTION, INC.

GRAND RAPIDS, MI 49544 www.meijer.com

principal display panel

NDC 79481-0782-6

meijer®

Castor Oil U.S.P.

Stimulant laxative

For the Relief of Occational Constipation

DO NOT USE IF SEAL UNDER CAP IS BROKEN OR MISSING.

4 FL OZ (118 mL)